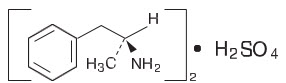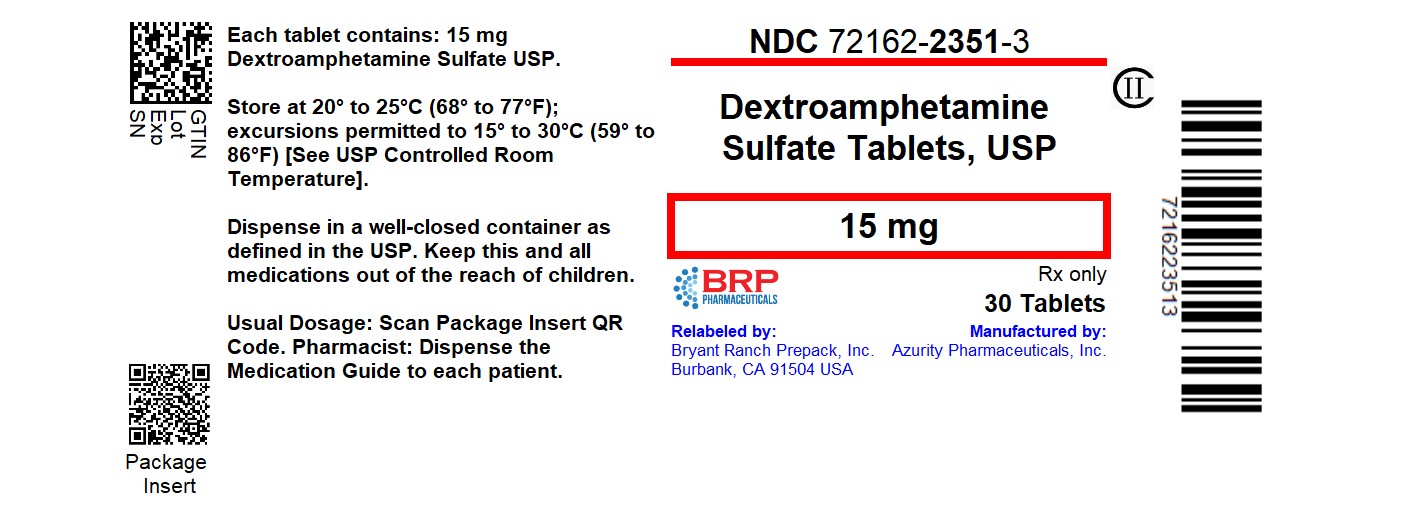 DRUG LABEL: Dextroamphetamine Sulfate
NDC: 72162-2351 | Form: TABLET
Manufacturer: Bryant Ranch Prepack
Category: prescription | Type: HUMAN PRESCRIPTION DRUG LABEL
Date: 20250826
DEA Schedule: CII

ACTIVE INGREDIENTS: DEXTROAMPHETAMINE SULFATE 15 mg/1 1
INACTIVE INGREDIENTS: SILICON DIOXIDE; CROSPOVIDONE (120 .MU.M); MICROCRYSTALLINE CELLULOSE; STEARIC ACID; FD&C BLUE NO. 1; FD&C BLUE NO. 2; FD&C RED NO. 40

Dextroamphetamine Sulfate Tablets, USP CII

WARNING: ABUSE, MISUSE, AND ADDICTION

Dextroamphetamine sulfate has a high potential for abuse and misuse, which can lead to the development of a substance use disorder, including addiction. Misuse and abuse of CNS stimulants, including dextroamphetamine sulfate, can result in overdose and death (see OVERDOSAGE), and this risk is increased with higher doses or unapproved methods of administration, such as snorting or injection.

Before prescribing dextroamphetamine sulfate, assess each patient's risk for abuse, misuse, and addiction. Educate patients and their families about these risks, proper storage of the drug, and proper disposal of any unused drug. Throughout dextroamphetamine sulfate treatment, reassess each patient's risk of abuse, misuse, and addiction and frequently monitor for signs and symptoms of abuse, misuse, and addiction (see WARNINGSand DRUG ABUSE and DEPENDENCE).

DESCRIPTION

Dextroamphetamine sulfate, USP is the dextro isomer of the compound d,l-amphetamine sulfate, a sympathomimetic amine of the amphetamine group. Chemically, dextroamphetamine is d-alpha-methylphenethylamine, and is present in all forms of dextroamphetamine sulfate, USP as the neutral sulfate. The structural formula is as follows:

(C9H13N)2∙H2SO4M.W.368.49

INACTIVE INGREDIENTS

Each tablet, for oral administration, contains dextroamphetamine sulfate, USP in either 5 mg, 10 mg, 15 mg, 20 mg or 30 mg. Each tablet also contains the following inactive ingredients: colloidal silicon dioxide, crospovidone, microcrystalline cellulose and stearic acid.

The 5 mg tablets also contain D&C Red #27 and FD&C Yellow #6. The 10 mg tablets also contain FD&C Red #40, FD&C Yellow #6 and FD&C Blue #2. The 15 mg tablets also contain FD&C Blue #1, FD&C Blue #2, and FD&C Red #40. The 20 mg tablets also contain FD&C Blue #1 and D&C Red #27. The 30 mg tablets also contain D&C Yellow #10.

CLINICAL PHARMACOLOGY

Amphetamines are non-catecholamine, sympathomimetic amines with CNS stimulant activity. Peripheral actions include elevations of systolic and diastolic blood pressures and weak bronchodilator and respiratory stimulant action.

There is neither specific evidence which clearly establishes the mechanism whereby amphetamines produce mental and behavioral effects in children, nor conclusive evidence regarding how these effects relate to the condition of the central nervous system.

Pharmacokinetics

The pharmacokinetics of the tablet and sustained-release capsule were compared in 12 healthy subjects. The extent of bioavailability of the sustained-release capsule was similar compared to the immediate-release tablet. Following administration of three 5 mg tablets, average maximal dextroamphetamine plasma concentrations (Cmax) of 36.6 ng/mL were achieved at approximately 3 hours. Following administration of one 15 mg sustained-release capsule, maximal dextroamphetamine plasma concentrations were obtained approximately 8 hours after dosing. The average Cmaxwas 23.5 ng/mL. The average plasma T½ was similar for both the tablet and sustained-release capsule and was approximately 12 hours.

In 12 healthy subjects, the rate and extent of dextroamphetamine absorption were similar following administration of the sustained-release capsule formulation in the fed (58 to 75 gm fat) and fasted state.

INDICATIONS AND USAGE

Dextroamphetamine sulfate tablets, USP are indicated for:

- Narcolepsy.
- Attention Deficit Disorder with Hyperactivity:As an integral part of a total treatment program which typically includes other remedial measures (psychological, educational, social) for a stabilizing effect in pediatric patients (ages 3 to 16 years) with a behavioral syndrome characterized by the following group of developmentally inappropriate symptoms: moderate to severe distractibility, short attention span, hyperactivity, emotional lability, and impulsivity. The diagnosis of this syndrome should not be made with finality when these symptoms are only of comparatively recent origin. Nonlocalizing (soft) neurological signs, learning disability, and abnormal EEG may or may not be present, and a diagnosis of central nervous system dysfunction may or may not be warranted.

CONTRAINDICATIONS

Known hypersensitivity to amphetamine products.

During or within 14 days following the administration of monoamine oxidase inhibitors (hypertensive crises may result).

WARNINGS

Abuse, Misuse, and Addiction

Dextroamphetamine sulfate has a high potential for abuse and misuse. The use of dextroamphetamine sulfate exposes individuals to the risks of abuse and misuse, which can lead to the development of a substance use disorder, including addiction. Amphetamine sulfate can be diverted for non-medical use into illicit channels or distribution (see DRUG ABUSE and DEPENDENCE). Misuse and abuse of CNS stimulants, including dextroamphetamine sulfate, can result in overdose and death (see OVERDOSAGE), and this risk is increased with higher doses or unapproved methods of administration, such as snorting or injection.

Before prescribing dextroamphetamine sulfate, assess each patient's risk for abuse, misuse, and addiction. Educate patients and their families about these risks and proper disposal of any unused drug. Advise patients to store amphetamine sulfate in a safe place, preferably locked, and instruct patients to not give dextroamphetamine sulfate to anyone else. Throughout dextroamphetamine sulfate treatment, reassess each patient's risk of abuse, misuse, and addiction and frequently monitor for signs and symptoms of abuse, misuse, and addiction.

Risks to Patients with Serious Cardiac Disease

Sudden death has been reported in patients with structural cardiac abnormalities or other serious cardiac disease who are treated with CNS stimulants at the recommended ADHD dosages.

Avoid dextroamphetamine sulfate use in patients with known structural cardiac abnormalities, cardiomyopathy, serious cardiac arrhythmia, coronary artery disease, or other serious cardiac disease.

Increased Blood Pressure and Heart Rate

CNS stimulants cause an increase in blood pressure (mean increase about 2 to 4 mm Hg) and heart rate (mean increase about 3 to 6 bpm). Monitor all patients for potential tachycardia and hypertension.

Psychiatric Adverse Reactions

Exacerbation of Pre-Existing Psychosis

CNS stimulants may exacerbate symptoms of behavior disturbance and thought disorder in patients with a pre-existing psychotic disorder.

Induction of a Manic Episode in Patients with Bipolar Disorder

CNS stimulants may induce a manic or mixed episode in patients. Prior to initiating treatment, screen patients for risk factors for developing a manic episode (e.g., comorbid or history of depressive symptoms or a family history of suicide, bipolar disorder, or depression).

New Psychotic or Manic Symptoms

CNS stimulants, at recommended doses, may cause psychotic or manic symptoms (e.g., hallucinations, delusional thinking, or mania) in patients without a prior history of psychotic illness or mania. In a pooled analysis of multiple short-term, placebo-controlled studies of CNS stimulants, psychotic or manic symptoms occurred in approximately 0.1% of CNS stimulant-treated patients, compared with 0% of placebo-treated patients. If such symptoms occur, consider discontinuing dextroamphetamine sulfate.

Long-Term Suppression of Growth in Pediatric Patients

CNS stimulants have been associated with weight loss and slowing of growth rate in pediatric patients, including dextroamphetamine sulfate. Closely monitor growth (weight and height) in dextroamphetamine sulfate -treated pediatric patients treated with CNS stimulants.

Pediatric patients who are not growing or gaining height or weight as expected may need to have their treatment interrupted (see PRECAUTIONS, PEDIATRIC USE).

Seizures

There is some clinical evidence that stimulants may lower the convulsive threshold in patients with prior history of seizures, in patients with prior EEG abnormalities in absence of seizures, and, very rarely, in patients without a history of seizures and no prior EEG evidence of seizures. In the presence of seizures, the drug should be discontinued.

Peripheral Vasculopathy, Including Raynaud's Phenomenon

Stimulants, including dextroamphetamine sulfate tablets, used to treat ADHD are associated with peripheral vasculopathy, including Raynaud's phenomenon. Signs and symptoms are usually intermittent and mild; however, very rare sequelae include digital ulcerations and/or soft tissue breakdown. Effects of peripheral vasculopathy, including Raynaud's phenomenon, were observed in post-marketing reports at the therapeutic dosages of CNS stimulants in all age groups throughout the course of treatment. Signs and symptoms generally improved after dosage reduction or discontinuation of the CNS stimulant. Careful observation for digital changes is necessary during dextroamphetamine sulfate tablet-treatment. Further clinical evaluation (e.g., rheumatology referral) may be appropriate for dextroamphetamine sulfate tablet-treated patients who develop signs or symptoms of peripheral vasculopathy.

Serotonin Syndrome

Serotonin syndrome, a potentially life-threatening reaction, may occur when amphetamines are used in combination with other drugs that affect the serotonergic neurotransmitter systems such as monoamine oxidase inhibitors (MAOIs), selective serotonin reuptake inhibitors (SSRIs), serotonin norepinephrine reuptake inhibitors (SNRIs), triptans, tricyclic antidepressants, fentanyl, lithium, tramadol, tryptophan, buspirone, and St. John's Wort (see Drug Interactions). The co-administration of cytochrome P450 (CYP2D6) inhibitors may also increase the risk with increased exposure to dextroamphetamine sulfate tablets. In these situations, consider an alternative non-serotonergic drug or an alternative drug that does not inhibit CYP2D6 (see Drug Interactions).

Serotonin syndrome symptoms may include mental status changes (e.g., agitation, hallucinations, delirium, and coma), autonomic instability (e.g., tachycardia, labile blood pressure, dizziness, diaphoresis, flushing, hyperthermia), neuromuscular symptoms (e.g., tremor, rigidity, myoclonus, hyperreflexia, incoordination), seizures, and/or gastrointestinal symptoms (e.g., nausea, vomiting, diarrhea).

Concomitant use of dextroamphetamine sulfate tablets with MAOI drugs is contraindicated (see CONTRAINDICATIONS).

Discontinue treatment with dextroamphetamine sulfate tablets and any concomitant serotonergic agents immediately if the above symptoms occur, and initiate supportive symptomatic treatment. If concomitant use of dextroamphetamine sulfate tablets with other serotonergic drugs or CYP2D6 inhibitors is clinically warranted, initiate dextroamphetamine sulfate tablets with lower doses, monitor patients for the emergence of serotonin syndrome during drug initiation or titration, and inform patients of the increased risk for serotonin syndrome.

Motor and Verbal Tics, and Worsening of Tourette's Syndrome

CNS stimulants, including dextroamphetamine sulfate, have been associated with the onset or exacerbation of motor and verbal tics. Worsening of Tourette's syndrome has also been reported. Assess the family history and clinically evaluate patients for tics or Tourette's syndrome before initiating dextroamphetamine sulfate. Regularly monitor patients for the emergence or worsening of tics or Tourette's syndrome with dextroamphetamine sulfate, and discontinue treatment if clinically appropriate.

PRECAUTIONS

Information for Patients

Advise the patient to read the FDA-approved patient labeling (Medication Guide).

Abuse, Misuse, and Addiction

Educate patients and their families about the risks of abuse, misuse, and addiction of dextroamphetamine sulfate, which can lead to overdose and death, and proper disposal of any unused drug (see WARNINGS, DRUG ABUSE AND DEPENDENCE, and OVERDOSAGE). Advise patients to store dextroamphetamine sulfate in a safe place, preferably locked, and instruct patients to not give dextroamphetamine sulfate to anyone else.

Risks to Patients with Serious Cardiac Disease

Advise patients that there are potential risks to patients with serious cardiac disease, including sudden death, with dextroamphetamine sulfate use. Instruct patients to contact a healthcare provider immediately if they develop symptoms such as exertional chest pain, unexplained syncope, or other symptoms suggestive of cardiac disease (see WARNINGS).

Increased Blood Pressure and Heart Rate

Advise patients that dextroamphetamine sulfate can elevate blood pressure and heart rate (see WARNINGS).

Psychiatric Adverse Reactions

Advise patients that dextroamphetamine sulfate, at recommended doses, can cause psychotic or manic symptoms, even in patients without prior history of psychotic symptoms or mania (see WARNINGS).

Long-Term Suppression of Growth in Pediatric Patients

Advise patients that dextroamphetamine sulfate, may cause slowing of growth including weight loss (see WARNINGS).

Circulation problems in fingers and toes [Peripheral vasculopathy, including Raynaud's phenomenon]

- Instruct patients beginning treatment with dextroamphetamine sulfate tablets about the risk of peripheral vasculopathy, including Raynaud's Phenomenon, and associated signs and symptoms: fingers or toes may feel numb, cool, painful, and/or may change color from pale, to blue, to red.
- Instruct patients to report to their physician any new numbness, pain, skin color change, or sensitivity to temperature in fingers or toes.
- Instruct patients to call their physician immediately with any signs of unexplained wounds appearing on fingers or toes while taking dextroamphetamine sulfate tablets.
- Further clinical evaluation (e.g., rheumatology referral) may be appropriate for certain patients.

Serotonin Syndrome

Caution patients about the risk of serotonin syndrome with concomitant use of dextroamphetamine sulfate and other serotonergic drugs including SSRIs, SNRIs, triptans, tricyclic antidepressants, fentanyl, lithium, tramadol, tryptophan, buspirone, St. John's Wort, and with drugs that impair metabolism of serotonin (in particular MAOIs, both those intended to treat psychiatric disorders and also others such as linezolid [see CONTRAINDICATIONS, WARNINGS, and DRUG INTERACTIONS]. Advise patients to contact their healthcare provider or report to the emergency room if they experience signs or symptoms of serotonin syndrome.

Motor and Verbal Tics, and Worsening of Tourette's Syndrome

Advise patients that motor and verbal tics and worsening of Tourette's Syndrome may occur during treatment with dextroamphetamine sulfate. Instruct the patients to notify their healthcare provider if emergence or worsening of tics or Tourette's syndrome occurs (see WARNINGS).

Amphetamines may impair the ability of the patient to engage in potentially hazardous activities such as operating machinery or vehicles; the patient should therefore be cautioned accordingly.

Drug Interactions

MAO Inhibitors

MAOI antidepressants, as well as a metabolite of furazolidone, slow amphetamine metabolism. This slowing potentiates amphetamines, increasing their effect on the release of norepinephrine and other monoamines from adrenergic nerve endings; this can cause headaches and other signs of hypertensive crisis. A variety of neurological toxic effects and malignant hyperpyrexia can occur, sometimes with fatal results.

Serotonergic Drugs

The concomitant use of dextroamphetamine sulfate tablets and serotonergic drugs increases the risk of serotonin syndrome. Initiate with lower doses and monitor patients for signs and symptoms of serotonin syndrome, particularly during dextroamphetamine sulfate tablets initiation or dosage increase. If serotonin syndrome occurs, discontinue dextroamphetamine sulfate tablets and the concomitant serotonergic drug(s) (see WARNINGSand PRECAUTIONS). Examples of serotonergic drugs include selective serotonin reuptake inhibitors (SSRI), serotonin norepinephrine reuptake inhibitors (SNRI), triptans, tricyclic antidepressants, fentanyl, lithium, tramadol, tryptophan, buspirone, St. John's Wort.

CYP2D6 Inhibitors

The concomitant use of dextroamphetamine sulfate tablets and CYP2D6 inhibitors may increase the exposure of dextroamphetamine sulfate tablets compared to the use of the drug alone and increase the risk of serotonin syndrome. Initiate with lower doses and monitor patients for signs and symptoms of serotonin syndrome particularly during dextroamphetamine sulfate tablets initiation and after a dosage increase. If serotonin syndrome occurs, discontinue dextroamphetamine sulfate tablets and the CYP2D6 inhibitor (see WARNINGS, OVERDOSAGE).

Acidifying Agents

Gastrointestinal acidifying agents (guanethidine, reserpine, glutamic acid HCl, ascorbic acid, fruit juices, etc.) lower absorption of amphetamines. Urinary acidifying agents (ammonium chloride, sodium acid phosphate, etc.) increase the concentration of the ionized species of the amphetamine molecule, thereby increasing urinary excretion. Both groups of agents lower blood levels and efficacy of amphetamines.

Adrenergic Blockers

Adrenergic blockers are inhibited by amphetamines.

Alkalinizing Agents

Gastrointestinal alkalinizing agents (sodium bicarbonate, etc.) increase absorption of amphetamines. Urinary alkalinizing agents (acetazolamide, some thiazides) increase the concentration of the non-ionized species of the amphetamine molecule, thereby decreasing urinary excretion. Both groups of agents increase blood levels and therefore potentiate the actions of amphetamines.

Antidepressants, Tricyclic

Amphetamines may enhance the activity of tricyclic or sympathomimetic agents; d-amphetamine with desipramine or protriptyline and possibly other tricyclics cause striking and sustained increases in the concentration of d-amphetamine in the brain; cardiovascular effects can be potentiated.

Antihistamines

Amphetamines may counteract the sedative effect of antihistamines.

Antihypertensives

Amphetamines may antagonize the hypotensive effects of antihypertensives.

Chlorpromazine

Chlorpromazine blocks dopamine and norepinephrine reuptake, thus inhibiting the central stimulant effects of amphetamines, and can be used to treat amphetamine poisoning.

Ethosuximide

Amphetamines may delay intestinal absorption of ethosuximide.

Haloperidol

Haloperidol blocks dopamine and norepinephrine reuptake, thus inhibiting the central stimulant effects of amphetamines.

Lithium Carbonate

The stimulatory effects of amphetamines may be inhibited by lithium carbonate.

Meperidine

Amphetamines potentiate the analgesic effect of meperidine.

Methenamine Therapy

Urinary excretion of amphetamines is increased, and efficacy is reduced, by acidifying agents used in methenamine therapy.

Norepinephrine

Amphetamines enhance the adrenergic effect of norepinephrine.

Phenobarbital

Amphetamines may delay intestinal absorption of phenobarbital; co-administration of phenobarbital may produce a synergistic anticonvulsant action.

Phenytoin

Amphetamines may delay intestinal absorption of phenytoin; co-administration of phenytoin may produce a synergistic anticonvulsant action.

Propoxyphene

In cases of propoxyphene overdosage, amphetamine CNS stimulation is potentiated and fatal convulsions can occur.

Veratrum Alkaloids

Amphetamines inhibit the hypotensive effect of veratrum alkaloids.

Drug/Laboratory Test Interactions

- Amphetamines can cause a significant elevation in plasma corticosteroid levels. This increase is greatest in the evening.
- Amphetamines may interfere with urinary steroid determinations.

Carcinogenesis/Mutagenesis

Mutagenicity studies and long-term studies in animals to determine the carcinogenic potential of dextroamphetamine sulfate have not been performed.

Pregnancy

Teratogenic Effects

Pregnancy Category C

Dextroamphetamine has been shown to have embryotoxic and teratogenic effects when administered to A/Jax mice and C57BL mice in doses approximately 41 times the maximum human dose. Embryotoxic effects were not seen in New Zealand white rabbits given the drug in doses 7 times the human dose nor in rats given 12.5 times the maximum human dose. While there are no adequate and well-controlled studies in pregnant women, there has been one report of severe congenital bony deformity, tracheoesophageal fistula, and anal atresia (Vater association) in a baby born to a woman who took dextroamphetamine sulfate with lovastatin during the first trimester of pregnancy. Dextroamphetamine should be used during pregnancy only if the potential benefit justifies the potential risk to the fetus.

Nonteratogenic Effects

Infants born to mothers dependent on amphetamines have an increased risk of premature delivery and low birth weight. Also, these infants may experience symptoms of withdrawal as demonstrated by dysphoria, including agitation, and significant lassitude.

Nursing Mothers

Amphetamines are excreted in human milk. Mothers taking amphetamines should be advised to refrain from nursing.

Pediatric Use

Long-term effects of amphetamines in pediatric patients have not been well established.

Amphetamines are not recommended for use in pediatric patients under 3 years of age with Attention Deficit Disorder with Hyperactivity described under INDICATIONS AND USAGE.

Clinical experience suggests that in psychotic pediatric patients, administration of amphetamines may exacerbate symptoms of behavior disturbance and thought disorder.

Amphetamines have been reported to exacerbate motor and phonic tics and Tourette's syndrome. Therefore, clinical evaluation for tics and Tourette's syndrome in pediatric patients and their families should precede use of stimulant medications.

Data are inadequate to determine whether chronic administration of amphetamines may be associated with growth inhibition; therefore, growth should be monitored during treatment.

Drug treatment is not indicated in all cases of Attention Deficit Disorder with Hyperactivity and should be considered only in light of the complete history and evaluation of the pediatric patient. The decision to prescribe amphetamines should depend on the physician's assessment of the chronicity and severity of the pediatric patient's symptoms and their appropriateness for his/her age. Prescription should not depend solely on the presence of one or more of the behavioral characteristics.

When these symptoms are associated with acute stress reactions, treatment with amphetamines is usually not indicated.

ADVERSE REACTIONS

Cardiovascular

Palpitations, tachycardia, elevation of blood pressure. There have been isolated reports of cardiomyopathy associated with chronic amphetamine use.

Central Nervous System

Psychotic episodes at recommended doses (rare), overstimulation, restlessness, dizziness, insomnia, euphoria, dyskinesia, dysphoria, tremor, headache, exacerbation of motor and verbal tics and Tourette's syndrome.

Gastrointestinal

Dryness of the mouth, unpleasant taste, diarrhea, constipation, intestinal ischemia, and other gastrointestinal disturbances. Anorexia and weight loss may occur as undesirable effects.

Allergic

Urticaria.

Endocrine

Impotence, changes in libido, frequent or prolonged erections.

Musculoskeletal

Rhabdomyolysis.

DRUG ABUSE AND DEPENDENCE

Dextroamphetamine sulfate tablets are a Schedule II controlled substance.

Abuse

Dextroamphetamine sulfate has a high potential for abuse and misuse which can lead to the development of a substance use disorder, including addiction (see WARNINGS). Dextroamphetamine sulfate can be diverted for non-medical use into illicit channels or distribution.

Abuse is the intentional non-therapeutic use of a drug, even once, to achieve a desired psychological or physiological effect. Misuse is the intentional use, for therapeutic purposes, of a drug by an individual in a way other than prescribed by a health care provider or for whom it was not prescribed. Drug addiction is a cluster of behavioral, cognitive, and physiological phenomena that may include a strong desire to take the drug, difficulties in controlling drug use (e.g., continuing drug use despite harmful consequences, giving a higher priority to drug use than other activities and obligations), and possible tolerance or physical dependence.

Misuse and abuse of amphetamines may cause increased heart rate, respiratory rate, or blood pressure; sweating; dilated pupils; hyperactivity; restlessness; insomnia; decreased appetite; loss of coordination; tremors; flushed skin; vomiting; and/or abdominal pain. Anxiety, psychosis, hostility, aggression, and suicidal or homicidal ideation have also been observed with CNS stimulants abuse and/or misuse. Misuse and abuse of CNS stimulants, including dextroamphetamine sulfate, can result in overdose and death (see OVERDOSAGE), and this risk is increased with higher doses or unapproved methods of administration, such as snorting or injection.

Dependence

Physical Dependence

Dextroamphetamine sulfate may produce physical dependence. Physical dependence is a state that develops as a result of physiological adaptation in response to repeated drug use, manifested by withdrawal signs and symptoms after abrupt discontinuation or a significant dose reduction of a drug.

Withdrawal signs and symptoms after abrupt discontinuation or dose reduction following prolonged use of CNS stimulants including dextroamphetamine sulfate include dysphoric mood; depression; fatigue; vivid, unpleasant dreams; insomnia or hypersomnia; increased appetite; and psychomotor retardation or agitation.

Tolerance

Dextroamphetamine sulfate may produce tolerance. Tolerance is a physiological state characterized by a reduced response to a drug after repeated administration (i.e., a higher dose of a drug is required to produce the same effect that was once obtained at a lower dose).

OVERDOSAGE

Clinical Effects of Overdose

Overdose of CNS stimulants is characterized by the following sympathomimetic effects:

- Cardiovascular effects including tachyarrhythmias, and hypertension or hypotension. Vasospasm, myocardial infarction, or aortic dissection may precipitate sudden cardiac death. Takotsubo cardiomyopathy may develop.
- CNS effects including psychomotor agitation, confusion, and hallucinations. Serotonin syndrome, seizures, cerebral vascular accidents, and coma may occur.
- Life-threatening hyperthermia (temperatures greater than 104°F) and rhabdomyolysis may develop.

Overdose Management

Consider the possibility of multiple drug ingestion. D-amphetamine is not dialyzable. Consider contacting the Poison Help line (1-800-222-1222) or a medical toxicologist for additional overdose management recommendations.

DOSAGE AND ADMINISTRATION

Amphetamines should be administered at the lowest effective dosage and dosage should be individually adjusted. Late evening doses should be avoided because of the resulting insomnia.

Narcolepsy

Usual dose is 5 to 60 mg per day in divided doses, depending on the individual patient response.

Narcolepsy seldom occurs in children under 12 years of age; however, when it does, dextroamphetamine sulfate may be used. The suggested initial dose for patients aged 6 to 12 is 5 mg daily; daily dose may be raised in increments of 5 mg at weekly intervals until optimal response is obtained. In patients 12 years of age and older, start with 10 mg daily; daily dosage may be raised in increments of 10 mg at weekly intervals until an optimal response is obtained. If bothersome adverse reactions appear (e.g., insomnia or anorexia), dosage should be reduced. Give first dose on awakening; additional doses (1 or 2) at intervals of 4 to 6 hours.

Attention Deficit Disorder with Hyperactivity

Not recommended for pediatric patients under 3 years of age.

In pediatric patients from 3 to 5 years of age,start with 2.5 mg daily; daily dosage may be raised in increments of 2.5 mg at weekly intervals until optimal response is obtained.

In pediatric patients 6 years of age and older,start with 5 mg once or twice daily; daily dosage may be raised in increments of 5 mg at weekly intervals until optimal response is obtained. Only in rare cases will it be necessary to exceed a total of 40 mg per day.

Give first dose on awakening; additional doses (1 or 2) at intervals of 4 to 6 hours.

Where possible, drug administration should be interrupted occasionally to determine if there is a recurrence of behavioral symptoms sufficient to require continued therapy.

Prior to treating patients with dextroamphetamine sulfate tablets assess:

- for the presence of cardiac disease (i.e., perform a careful history, family history of sudden death or ventricular arrhythmia, and physical exam) (see WARNINGS).
- the family history and clinically evaluate patients for motor or verbal tics or Tourette's syndrome (see WARNINGS).

HOW SUPPLIED

Dextroamphetamine sulfate tablets, USP are supplied as follows:

15 mg - Light blue, pentagon tablet, debossed "15" on one side and "MIA" on the other side.

- NDC 72162-2351-3: 30 Tablets in a BOTTLE

Store at 20° to 25°C (68° to 77°F); excursions permitted 15° to 30°C (59° to 86°F). [See USP Controlled Room Temperature]

Dispense in a tight, light-resistant container as defined in the USP, with a child-resistant closure (as required).

KEEP THIS AND ALL MEDICATIONS OUT OF THE REACH OF CHILDREN.

Repackaged/Relabeled by:
Bryant Ranch Prepack, Inc.
Burbank, CA 91504

DEA Order Form Required.

Pharmacist: Medication Guide to be dispensed to Patients.

Manufactured for:
Wilshire Pharmaceuticals, Inc.
Atlanta, GA 30328

DEX-PI-12 Rev. MAR2024

MEDICATION GUIDE
Dextroamphetamine Sulfate Tablets, USP CII
(dex" troe am fet´ a meen sul´ fate)

What is the most important information I should know about dextroamphetamine sulfate tablets?
Dextroamphetamine sulfate tablets may cause serious side effects, including:

- Abuse, misuse, and addiction. Dextroamphetamine sulfate tablets have a high chance for abuse and misuse and may lead to substance use problems, including addiction. Misuse and abuse of dextroamphetamine sulfate tablets, other-amphetamine containing medicines, and methylphenidate containing medicines, can lead to overdose and death. The risk of overdose and death is increased with higher doses of dextroamphetamine sulfate tablets or when they are used in ways that are not approved, such as snorting or injection.
  - Your healthcare provider should check you or your child's risk for abuse, misuse, and addiction before starting treatment with dextroamphetamine sulfate tablets and will monitor you or your child during treatment.
  - Dextroamphetamine sulfate tablets may lead to physical dependence after prolonged use, even if taken as directed by your healthcare provider.
  - Do not give dextroamphetamine sulfate tablets to anyone else. See " What are dextroamphetamine sulfate tablets?" for more information.
  - Keep dextroamphetamine sulfate tablets in a safe place and properly dispose of any unused medicine. See " How should I store dextroamphetamine sulfate tablets?" for more information.
  - Tell your healthcare provider if you or your child have ever abused or been dependent on alcohol, prescription medicines, or street drugs.
- Risks for people with serious heart disease: Sudden death has happened in people who have heart defects or other serious heart disease.
  Your healthcare provider should check you or your child carefully for heart problems before starting treatment with dextroamphetamine sulfate tablets. Tell your healthcare provider if you or your child have any heart problems, heart disease, or heart defects.
  Call your healthcare provider right away or go to the nearest hospital emergency room right away if you or your child have any signs of heart problems such as chest pain, shortness of breath, or fainting during treatment with dextroamphetamine sulfate tablets.
- Increased blood pressure and heart rate.
  Your healthcare provider should check you or your child's blood pressure and heart rate regularly during treatment with dextroamphetamine sulfate tablets.
- Mental (psychiatric) problems, including:
  - new or worse behavior or thought problems.
  - new or worse bipolar illness.
  - new psychotic symptoms (such as hearing voices or seeing or believing things that are not real) or new manic symptoms.
  Tell your healthcare provider about any mental problems you or your child have, or about a family history of suicide, bipolar illness, or depression.
  Call your healthcare provider right away if you or your child have any new or worsening mental symptoms or problems during treatment with dextroamphetamine sulfate tablets, especially hearing voices, seeing or believing things that are not real, or new manic symptoms.

What are dextroamphetamine sulfate tablets?
Dextroamphetamine sulfate tablets are central nervous system (CNS) stimulant prescription medicines used for the treatment of:

- a sleep disorder called narcolepsy.
- Attention-Deficit Hyperactivity Disorder (ADHD) in children 3 to 16 years of age. Dextroamphetamine sulfate tablets may help increase attention and decrease impulsiveness and hyperactivity in people with ADHD.

It is not known if dextroamphetamine sulfate tablets are safe and effective in children under 3 years of age.
Dextroamphetamine sulfate is a federally controlled substance (CII) because it contains dextroamphetamine that can be a target for people who abuse prescription medicines or street drugs. Keep dextroamphetamine sulfate tablets in a safe place to protect it from theft. Never give your dextroamphetamine sulfate tablets to anyone else because they may cause death or harm them. Selling or giving away dextroamphetamine sulfate tablets may harm others and is against the law.

Do not take dextroamphetamine sulfate tablets if you or your child:

- are allergic to amphetamine products or any of the ingredients in dextroamphetamine sulfate tablets. See the end of this Medication Guide for a complete list of ingredients in dextroamphetamine sulfate tablets.
- are taking or have taken within the past 14 days, a medicine used to treat depression called a monoamine oxidase inhibitor (MAOI), including the antibiotic linezolid or the intravenous medicine methylene blue.

Before taking dextroamphetamine sulfate tablets, tell your healthcare provider about all of your or your child's medical conditions, including if you or your child:

- have heart problems, heart disease, heart defects, or high blood pressure.
- have mental problems including psychosis, mania, bipolar illness, or depression, or have a family history of suicide, bipolar illness, or depression.
- have seizures or have had an abnormal brain wave test (EEG).
- have circulation problems in fingers and toes.
- have or had repeated movements or sounds (tics) or Tourette's syndrome, or have a family history of tics or Tourette's syndrome.
- are pregnant or plan to become pregnant. It is not known if dextroamphetamine sulfate tablets will harm the unborn baby. Tell your healthcare provider if you or your child become pregnant during treatment with dextroamphetamine sulfate tablets.
- are breastfeeding or plan to breastfeed. Dextroamphetamine sulfate tablets passes into breast milk. You or your child should not breastfeed during treatment with dextroamphetamine sulfate tablets. Talk to your healthcare provider about the best way to feed the baby during treatment with dextroamphetamine sulfate tablets.

Tell your healthcare provider about all of the medicines that you or your child take, including prescription and over-the-counter medicines, vitamins, and herbal supplements.
Dextroamphetamine sulfate tablets and some medicines may interact with each other and cause serious side effects. Sometimes the doses of other medicines will need to be changed during treatment with dextroamphetamine sulfate tablets. Your healthcare provider will decide if dextroamphetamine sulfate tablets can be taken with other medicines.
Especially tell your healthcare provider if you or your child take:

- selective serotonin reuptake inhibitors (SSRIs)
- medicines used to treat migraine headaches called triptans
- lithium
- tramadol
- buspirone

- serotonin norepinephrine reuptake inhibitors (SNRIs)
- tricyclic antidepressants
- fentanyl
- tryptophan
- St. John's Wort

Know the medicines that you or your child take. Keep a list of your or your child's medicines with you to show your healthcare provider and pharmacist when you or your child get a new medicine. Do not start any new medicine during treatment with dextroamphetamine sulfate tablets without talking to your healthcare provider first.

How should dextroamphetamine sulfate tablets be taken?

- Take dextroamphetamine sulfate tablets exactly as prescribed by your or your child's healthcare provider.
- Your healthcare provider may change the dose if needed.
- Dextroamphetamine sulfate tablets is usually taken two to three times a day. The first dose is usually taken in the morning. One or two more doses may be taken during the day, 4 to 6 hours apart.

If you or your child take too much dextroamphetamine sulfate tablets, call your healthcare provider or Poison Help line at 1-800-222-1222 or go to the nearest hospital emergency room right away.

What should I avoid while taking dextroamphetamine sulfate tablets?
Do not drive, operate heavy machinery, or do other potentially dangerous activities until you know how dextroamphetamine sulfate tablets affects you.

What are possible side effects of dextroamphetamine sulfate tablets?
Dextroamphetamine sulfate tablets may cause serious side effects, including:

- See " What is the most important information I should know about dextroamphetamine sulfate tablets?"
- Slowing of growth (height and weight)in children. Children should have their height and weight checked often during treatment with dextroamphetamine sulfate tablets. Your healthcare provider may stop your child's dextroamphetamine sulfate tablets treatment if they are not growing or gaining weight as expected.
- Seizures. Your healthcare provider may stop treatment with Adderall if you or your child have a seizure.
- Circulation problems in fingers and toes (peripheral vasculopathy, including Raynaud's phenomenon). Signs and symptoms may include:
  - fingers or toes may feel numb, cool, painful.
  - fingers or toes may change color from pale, to blue, to red.
  Tell your healthcare provider if you or your child have numbness, pain, skin color change, or sensitivity to temperature in your fingers or toes.
  Call your healthcare provider right away if you or your child have any signs of unexplained wounds appearing on fingers or toes during treatment with dextroamphetamine sulfate tablets.
- New or worsening tics or worsening Tourette's syndrome. Tell your healthcare provider if you or your child get any new or worsening tics or worsening Tourette's syndrome during treatment with dextroamphetamine sulfate tablets.
- Serotonin syndrome. This problem may happen when dextroamphetamine sulfate tablets are taken with certain other medicines and may be life-threatening. Stop taking dextroamphetamine sulfate tablets and call your healthcare provider or go to the nearest hospital emergency room right away if you or your child develop any of the following signs and symptoms of serotonin syndrome:

- agitation
- fast heartbeat
- flushing
- seizures
- coma
- sweating
- loss of coordination

- confusion
- dizziness
- tremors, stiff muscles, or muscle twitching
- seeing or hearing things that are not real (hallucination)
- changes in blood pressure
- high body temperature (hypothermia)
- nausea, vomiting, diarrhea

The most common side effects of dextroamphetamine sulfate tablets include:

- fast heartbeat
- decreased appetite
- tremors

- headache
- trouble sleeping
- dizziness

- stomach upset
- weight loss
- dry mouth

These are not all of the possible side effects of dextroamphetamine sulfate tablets.
Call your doctor for medical advice about side effects. You may report side effects to FDA at 1-800-FDA-1088.
You may also report side effects to Wilshire Pharmaceuticals, Inc. at 1-877-495-6856.

How should I store dextroamphetamine sulfate tablets?

- Store dextroamphetamine sulfate tablets at room temperature between 68° to 77°F (20° to 25°C).
- Store dextroamphetamine sulfate tablets in a safe place, like a locked cabinet. Protect from light.
- Dispose of remaining, unused, or expired dextroamphetamine sulfate tablets by a medicine take back program at a U.S. Drug Enforcement Administration (DEA) authorized collection site. If no take back program or DEA authorized collector is available, mix dextroamphetamine sulfate tablets with an undesirable, nontoxic substance such as dirt, cat litter, or used coffee grounds to make it less appealing to children and pets. Place the mixture in a container such as a sealed plastic bag and throw away dextroamphetamine sulfate tablets in the household trash. Visit www.fda.gov/drugdisposal for additional information on disposal of unused medicines.

Keep dextroamphetamine sulfate tablets and all medicines out of the reach of children.

General information about the safe and effective use of dextroamphetamine sulfate tablets.
Medicines are sometimes prescribed for purposes other than those listed in a Medication Guide. Do not use dextroamphetamine sulfate tablets for a condition for which they were not prescribed. Do not give dextroamphetamine sulfate tablets to other people, even if they have the same symptoms that you or your child have. It may harm them and it is against the law. You can ask your pharmacist or healthcare provider for information about dextroamphetamine sulfate tablets that is written for health professionals. For more information about dextroamphetamine sulfate tablets you may also contact Wilshire Pharmaceuticals, Inc. at 1-877-495-6856.

What are the ingredients in dextroamphetamine sulfate tablets?
Active ingredient: dextroamphetamine sulfate
Inactive ingredients: colloidal silicon dioxide, crospovidone, microcrystalline cellulose and stearic acid. The 5 mg tablets contain D&C Red #27 and FD&C Yellow #6. The 7.5 mg tablets contain FD&C Blue #1 and D&C Yellow #10. The 10 mg tablets contain FD&C Red #40, FD&C Yellow #6 and FD&C Blue #2. The 15 mg tablets contain FD&C Blue #1, FD&C Blue #2, and FD&C Red #40. The 20 mg tablets contain FD&C Blue #1 and D&C Red #27. The 30 mg tablets also contain D&C Yellow #10.
Manufactured for:
WILSHIRE®
PHARMACEUTICALS, INC
Rev. 11/2023
DEX-MG-09

This Medication Guide has been approved by the U.S. Food and Drug Administration.

PACKAGE LABEL

Dextroamphetamine Sulfate Tablets 15 mg (CII)